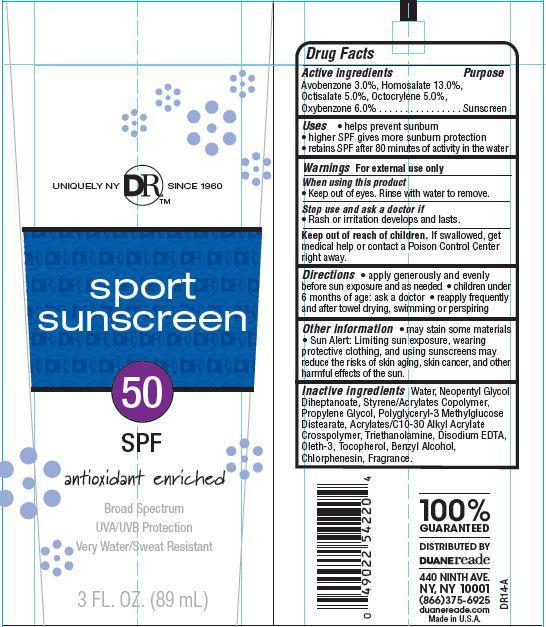 DRUG LABEL: Duane Reade Sport Sunscreen
NDC: 67732-410 | Form: LOTION
Manufacturer: DUANE READE INC.
Category: otc | Type: HUMAN OTC DRUG LABEL
Date: 20121114

ACTIVE INGREDIENTS: AVOBENZONE 3 g/100 g; HOMOSALATE 13 g/100 g; OCTISALATE 5 g/100 g; OCTOCRYLENE 5 g/100 g; OXYBENZONE 6 g/100 g
INACTIVE INGREDIENTS: WATER; NEOPENTYL GLYCOL DIHEPTANOATE; STEARIC ACID; TROLAMINE; PROPYLENE GLYCOL; BENZYL ALCOHOL; CARBOMER COPOLYMER TYPE A (ALLYL PENTAERYTHRITOL CROSSLINKED); OLETH-3; CHLORPHENESIN; TOCOPHEROL; EDETATE DISODIUM

Drug Facts

Active Ingredients

Avobenzone 3.0 %

Homosalate 13.0%

Octisalate 5.0%

Octocrylene 5.0%

Oxybenzone 6.0%

Purpose

Sunscreen

Uses

- helps prevent sunburn
- higher SPF gives more sunburn protection
- retains SPF after 80 minutes of activity in the water

Warnings

For external use only

When using this product

- keep out of eyes. Rinse with water to remove.

stop use and ask a doctor if

- rash or irritation develops and lasts

keep out of reach of children

If swallowed, get medical help or contact a Poison Control Center right away.

Directions

- apply generously and evenly before sun exposure and as needed
- children under 6 months of age:ask a doctor
- reapply frequently after towel drying, swimming or perspiring

Other Information

- may stain some materials
- Sun Alert: Limiting sun exposure, wearing, protective clothing, and using sunscreens may reduce the risks of skin aging, skin cancer, and other harmful effects of the sun.

Inactive Ingredients

Water, Neopentyl Glycol Diheptanoate, Styrene/Acrylates Copolymer,Propylene Glycol, Acrylates/C10-30 Alkyl Acrylate Crosspolymer, Triethanolamine, Disodium EDTA, Oleth-3, Tocopherol, Benzyl Alcohol, Chlorphenesin, Fragrance.

Principal Display Panel

UNIQUELY NY DRTM SINCE 1960

sport

sunscreen

50

SPF

antioxidant enriched

Broad Spectrum

UVA/UVB Protection

Very Water/Sweat Resistant

3 FL. OZ. (89mL)